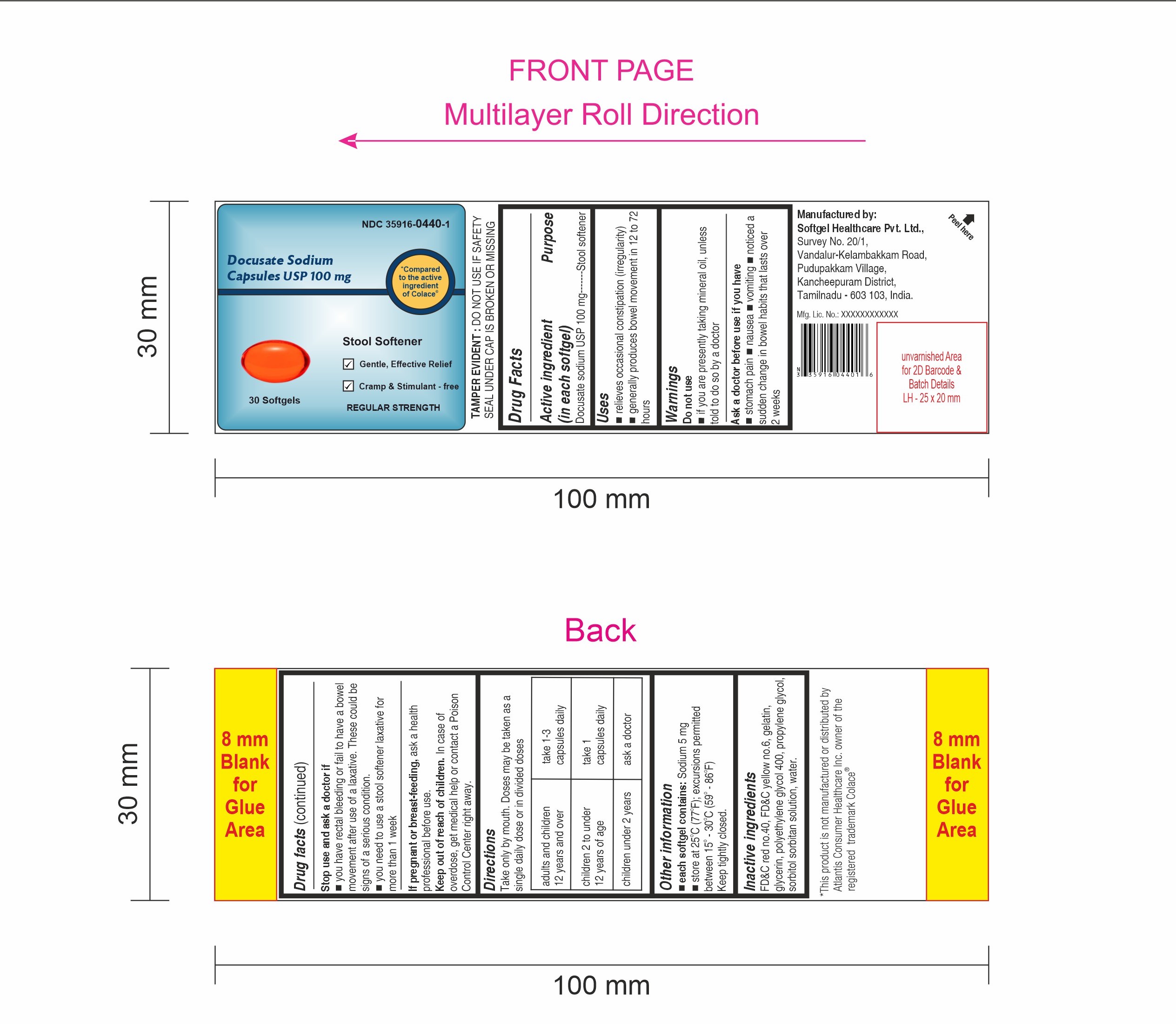 DRUG LABEL: Docusate Sodium
NDC: 35916-0440 | Form: CAPSULE, LIQUID FILLED
Manufacturer: Softgel Healthcare Pvt Ltd
Category: otc | Type: HUMAN OTC DRUG LABEL
Date: 20240831

ACTIVE INGREDIENTS: DOCUSATE SODIUM 100 mg/1 1
INACTIVE INGREDIENTS: SORBITOL; POLYETHYLENE GLYCOL 400; WATER; FD&C RED NO. 40; PROPYLENE GLYCOL; GELATIN; FD&C YELLOW NO. 6; GLYCERIN

Docusate Sodium Capsules USP 100 mg

Active ingredient (in each softgel)

Docusate Sodium USP 100 mg

Purpose

Stool softener

Uses

- relieves occasional constipation (irregularity)
- generally produces bowel movement in 12 to 72 hours

Warnings

Do not use

- if you are presently taking mineral oil, unless told to do so by a doctor

Ask a doctor before use if you have

- stomach pain
- nausea
- vomiting
- noticed a sudden change in bowel habits that last over 2 weeks

Stop use and ask a doctor if

- you have rectal bleeding or fail to have a bowel movement after use of a laxative. These could be signs of a serious condition.
- you need to use a stool softener laxative for more than 1 week

If pregnant or breast-feeding,

ask a health professional before use.

Keep out of reach of children

In case of overdose, get medical help or contact a Poison Control Center right away.

Directions

Take only by mouth. Doses may be taken as a single daily dose or in divided doses.

adults and children 12 years and over | take 1-3 capsules daily
children 2 to under 12 years of age | take 1 capsule daily
children under 2 years | ask a doctor

Other information

- each softgel contains: Sodium 5 mg
- store at 25°C (77°F); excursion permitted between 15°-30°C (59°-86°F).

Keep tightly closed.

Inactive ingredient

FD&C red no.40, FD&C yellow no.6, gelatin, glycerin, polyethylene glycol 400, propylene glycol, sorbitol sorbitan solution, water.

TAMPER EVIDENT

Do not use if safety seal under cap is broken or missing

Manufactured by

Softgel Healthcare Pvt. Ltd.,

Survey No. 20/1,

Vandalur-Kelambakkam Road,

Pudupakkam Village,

Kancheepuram District,

Tamilnadu - 603 103, India.

Mfg. Lic. No.: XXXXXXXXXXXX